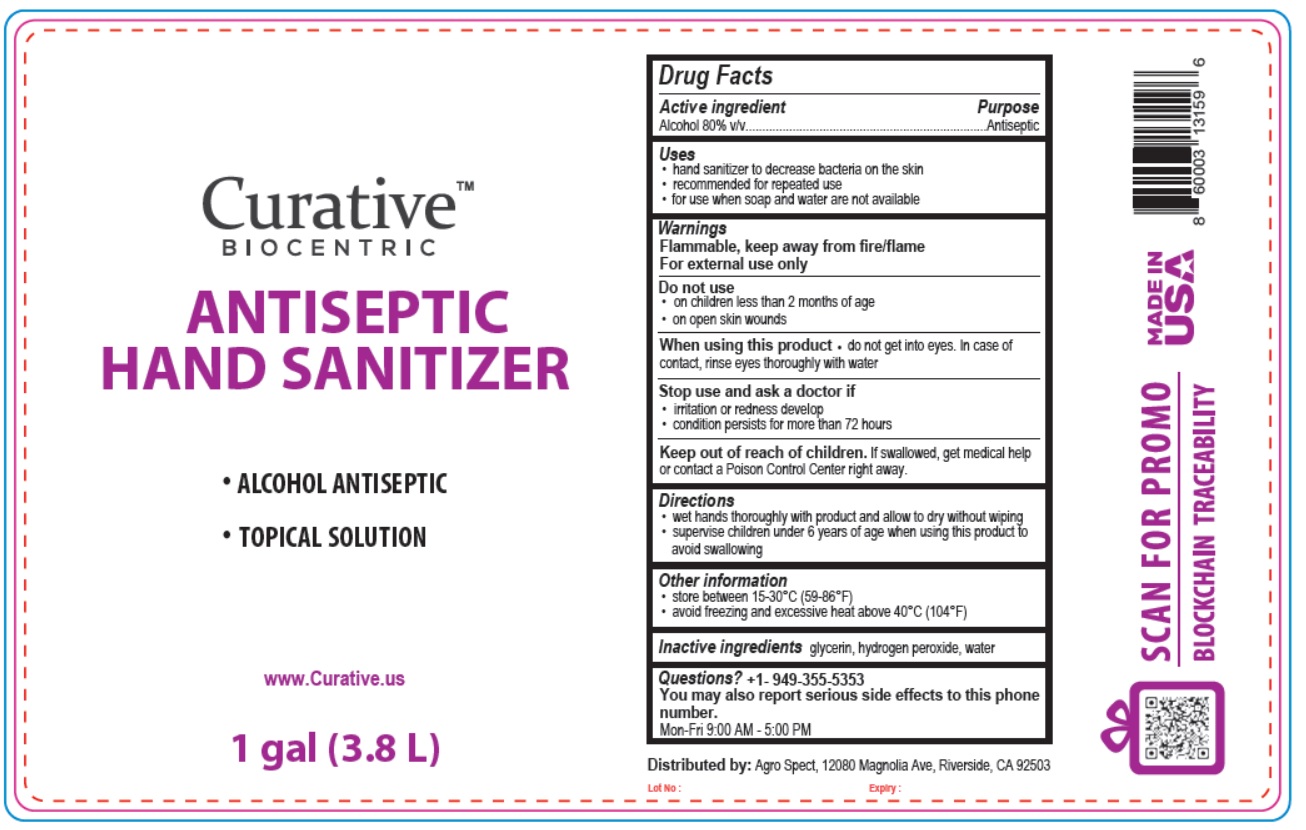 DRUG LABEL: Curative Biocentric Antiseptic Hand Sanitizer
NDC: 77094-200 | Form: SOLUTION
Manufacturer: Circular Centric Inc.
Category: otc | Type: HUMAN OTC DRUG LABEL
Date: 20200529

ACTIVE INGREDIENTS: ALCOHOL 80 mL/100 mL
INACTIVE INGREDIENTS: GLYCERIN; HYDROGEN PEROXIDE; WATER

CurativeTM BIOCENTRIC ANTISEPTIC HAND SANITIZER

Active ingredient

Alcohol 80% v/v

Purpose

Antiseptic

Uses

- hand sanitizer to decrease bacteria on the skin
- recommended for repeated use
- for use when soap and water are not available

Warnings

Flammable, keep away from fire/flame
For external use only

Do not use

- on children less than 2 months of age
- on open skin wounds

When using this product • do not get into eyes. In case of contact, rinse eyes thoroughly with water

Stop use and ask a doctor if

- irritation or redness develop
- condition persists for more than 72 hours

Keep out of reach of children. If swallowed, get medical help or contact a Poison Control Center right away.

Directions

- wet hands thoroughly with product and allow to dry without wiping
- supervise children under 6 years of age when using this product to avoid swallowing

Other information

- store between 15-30°C (59-86°F)
- avoid freezing and excessive heat above 40°C (104°F)

Inactive ingredients glycerin, hydrogen peroxide, water

Questions? +1- 949-355-5353

You may also report serious side effects to this phone number.

Mon-Fri 9:00 AM - 5:00 PM

- ALCOHOL ANTISEPTIC
- TOPICAL SOLUTION

www.Curative.us

Distributed by: Agro Spect, 12080 Magnolia Ave, Riverside, CA 92503

SCAN FOR PROMO

BLOCKCHAIN TRACEABILITY

MADE IN USA